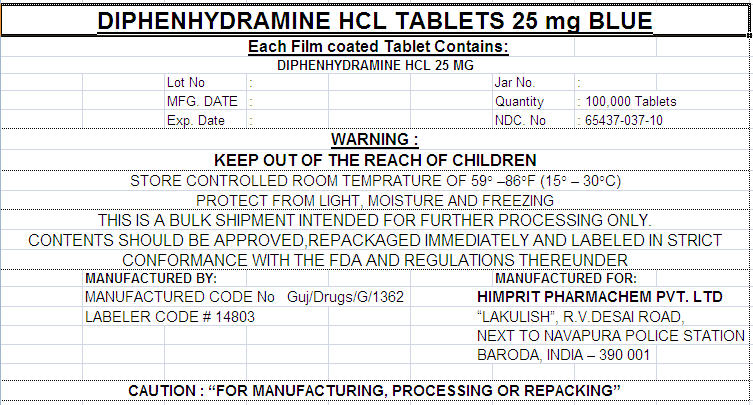 DRUG LABEL: DIPHENHYDRAMINE HYDROCHLORIDE
NDC: 65437-037 | Form: TABLET, FILM COATED
Manufacturer: HIMPRIT PHARMACHEM PVT LTD
Category: otc | Type: HUMAN OTC DRUG LABEL
Date: 20100203

ACTIVE INGREDIENTS: DIPHENHYDRAMINE HYDROCHLORIDE 25 mg/1 1
INACTIVE INGREDIENTS: CELLULOSE, MICROCRYSTALLINE; SILICON DIOXIDE; ANHYDROUS DIBASIC CALCIUM PHOSPHATE; CROSCARMELLOSE SODIUM; MAGNESIUM STEARATE; POLYETHYLENE GLYCOL; POLYVINYL ALCOHOL; TITANIUM DIOXIDE; WATER; D&C RED NO. 27

DIPHENHYDRAMINE HCL TABLETS 25 mg BLUE

Drug Facts

Active ingredient (in each caplet)

Diphenhydramine HCl 25 mg

Purpose

Nighttime sleep aid

Use

relief of occasional sleeplessness

Warnings

Do not use

- in children under 12 years of age
- with any other product containing diphenhydramine, even one used on skin

Ask a doctor before use if you have

- a breathing problem such as emphysema or chronic bronchitis
- trouble urinating due to an enlarged prostate gland
- glaucoma

Ask a doctor or pharmacist before use if you are taking sedatives or tranquilizers

When using this product

- avoid alcoholic drinks
- drowsiness will occur
- do not drive a motor vehicle or operate machinery

Stop use and ask a doctor if

- sleeplessness persists continuously for more than 2 weeks. Insomnia may be a symptom of serious underlying medical illness.

PREGNANCY OR BREAST FEEDING

If pregnant or breast-feeding, ask a health professional before use.

Keep out of reach of children.

DOSAGE AND ADMINISTRATION

Overdose warning: In case of overdose get medical help or contact a Poison Control Center right away.

Directions

adults and children 12 years and over | take 2 caplets at bedtime if needed or as directed by a doctor
children under 12 years | do not use

Other information

- each caplet contains: calcium 20 mg
- store between 20-25°C (68-77°F)
- do not use if carton is opened or blister unit is broken
- see side panel for lot number and expiration date

Inactive ingredients

carnauba wax, cellulose, croscarmellose sodium dibasic calcium phosphate, FD&C blue #1, hypromellose, magnesium stearate, polyethylene glycol, polysorbate 80, titanium dioxide

PRINCIPAL DISPLAY PANEL - 25 mg Label

DIPHENHYDRAMINE HCL TABLETS 25 mg BLUE
Each Film coated Tablet Contains:
DIPHENHYDRAMINE HCL 25 MG

Lot No | : |  |  | Jar No. | :
MFG. DATE | : |  |  | Quantity | : 100,000 Tablets
Exp. Date | : |  |  | NDC. No | : 65437-037-10

WARNING :
KEEP OUT OF THE REACH OF CHILDREN
STORE CONTROLLED ROOM TEMPRATURE OF 59° –86°F (15° – 30°C)
PROTECT FROM LIGHT, MOISTURE AND FREEZING
THIS IS A BULK SHIPMENT INTENDED FOR FURTHER PROCESSING ONLY.
CONTENTS SHOULD BE APPROVED,REPACKAGED IMMEDIATELY AND LABELED IN STRICT
CONFORMANCE WITH THE FDA AND REGULATIONS THEREUNDER

MANUFACTURED BY:
MANUFACTURED CODE No Guj/Drugs/G/1362
LABELER CODE # 14803

MANUFACTURED FOR:
HIMPRIT PHARMACHEM PVT. LTD
"LAKULISH", R.V.DESAI ROAD,
NEXT TO NAVAPURA POLICE STATION
BARODA, INDIA – 390 001

CAUTION : "FOR MANUFACTURING, PROCESSING OR REPACKING"